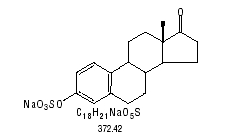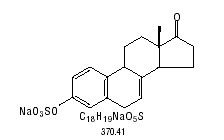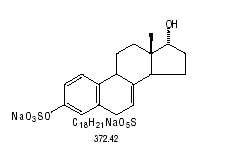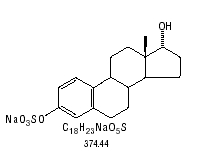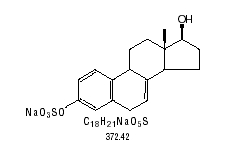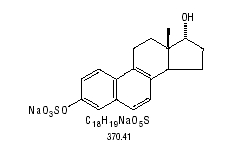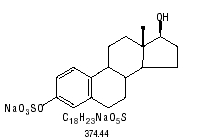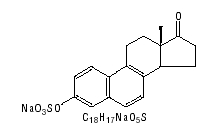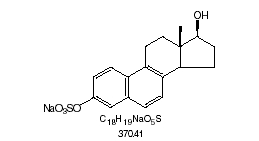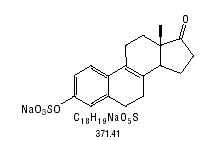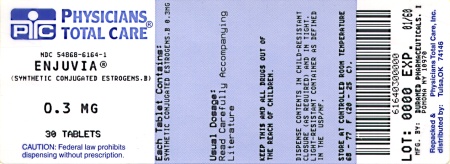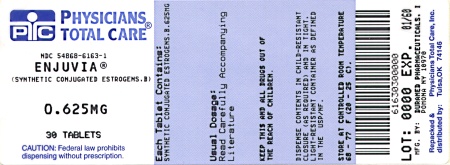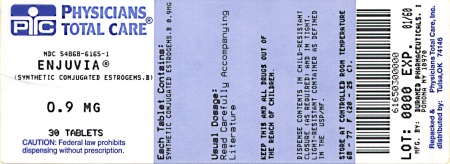 DRUG LABEL: ENJUVIA
NDC: 54868-6165 | Form: TABLET
Manufacturer: Physicians Total Care, Inc.
Category: prescription | Type: HUMAN PRESCRIPTION DRUG LABEL
Date: 20100301

ACTIVE INGREDIENTS: ESTROGENS, CONJUGATED SYNTHETIC B 0.9 mg/1 1
INACTIVE INGREDIENTS: ASCORBYL PALMITATE; BUTYLATED HYDROXYANISOLE; SILICON DIOXIDE; D&C YELLOW NO. 10; EDETATE DISODIUM; FD&C BLUE NO. 1; FD&C YELLOW NO. 6; GLYCERIN; HYPROMELLOSE; FERRIC OXIDE RED; LACTOSE MONOHYDRATE; MAGNESIUM STEARATE; ETHYLCELLULOSE; POLYETHYLENE GLYCOL; POLYSORBATE 80; WATER; TITANIUM DIOXIDE; TRIETHYL CITRATE; TRIACETIN

ENJUVIA®
(synthetic conjugated estrogens, B) Tablets

11001651

Rx only

ESTROGENS INCREASE THE RISK OF ENDOMETRIAL CANCER

Close clinical surveillance of all women taking estrogens is important. Adequate diagnostic measures, including endometrial sampling when indicated, should be undertaken to rule out malignancy in all cases of undiagnosed persistent or recurring abnormal vaginal bleeding. There is no evidence that the use of “natural” estrogens results in a different endometrial risk profile than synthetic estrogens at equivalent estrogen doses. (See WARNINGS, Malignant neoplasms, Endometrial cancer.)

CARDIOVASCULAR AND OTHER RISKS

Estrogens with or without progestins should not be used for the prevention of cardiovascular disease or dementia. (See CLINICAL STUDIES and WARNINGS, Cardiovascular disorders and Dementia.)

The estrogen alone substudy of the Women’s Health Initiative (WHI) reported increased risks of stroke and deep vein thrombosis (DVT) in postmenopausal women (50 to 79 years of age) during 6.8 years and 7.1 years, respectively, of treatment with oral conjugated estrogens (CE 0.625 mg) alone per day, relative to placebo. (See CLINICAL STUDIES and WARNINGS, Cardiovascular disorders.)

The estrogen-plus-progestin substudy of the WHI reported increased risks of myocardial infarction, stroke, invasive breast cancer, pulmonary emboli, and deep vein thrombosis in postmenopausal women (50 to 79 years of age) during 5.6 years of treatment with oral conjugated estrogens (CE 0.625 mg) combined with medroxyprogesterone acetate (MPA 2.5 mg) per day, relative to placebo. (See CLINICAL STUDIES, and WARNINGS, Cardiovascular disorders and Malignant neoplasms, Breast cancer).

The Women’s Health Initiative Memory Study (WHIMS), a substudy of WHI study, reported increased risk of developing probable dementia in postmenopausal women 65 years of age or older during 5.2 years of treatment with CE 0.625 mg alone and during 4 years of treatment with CE 0.625 mg combined with MPA 2.5 mg, relative to placebo. It is unknown whether this finding applies to younger postmenopausal women. (See CLINICAL STUDIES, WARNINGS, Dementia and PRECAUTIONS, Geriatric Use.)

Other doses of conjugated estrogens and medroxyprogesterone acetate, and other combinations and dosage forms of estrogens and progestins, were not studied in the WHI clinical trials, and in the absence of comparable data, these risks should be assumed to be similar. Because of these risks, estrogens with or without progestins should be prescribed at the lowest effective doses and for the shortest duration consistent with treatment goals and risks for the individual woman.

DESCRIPTION

ENJUVIA® (synthetic conjugated estrogens, B) tablets contain a blend of ten (10) synthetic estrogenic substances. The estrogenic substances are: sodium estrone sulfate, sodium equilin sulfate, sodium 17α-dihydroequilin sulfate, sodium 17α-estradiol sulfate, sodium 17β-dihydroequilin sulfate, sodium 17α-dihydroequilenin sulfate, sodium 17β-dihydroequilenin sulfate, sodium equilenin sulfate, sodium 17β-estradiol sulfate, and sodium Δ^8,9-dehydroestrone sulfate.

The structural formulae for these estrogens are:

Sodium Estrone Sulfate
Sodium Equilin Sulfate
Sodium 17α-Dihydroequilin Sulfate
Sodium 17α-Estradiol Sulfate
Sodium 17β-Dihydroequilenin Sulfate
Sodium 17α-Dihydroequilenin Sulfate
Sodium 17β-Estradiol Sulfate
Sodium Equilenin Sulfate
Sodium 17β-Dihydroequilenin Sulfate
Sodium Δ^8,9 dehydroestrone Sulfate

ENJUVIA tablets for oral administration are available in 0.3 mg, 0.45 mg, 0.625 mg, 0.9 mg and 1.25 mg strengths of synthetic conjugated estrogens, B. These tablets contain the following inactive ingredients: ascorbyl palmitate, butylated hydroxyanisole, colloidal silicon dioxide, edetate disodium dehydrate, plasticized ethylcellulose, hypromellose, lactose monohydrate, magnesium stearate, purified water, iron oxide red, titanium dioxide, polyethylene glycol, polysorbate 80, triacetate and triacetin/glycerol. In addition, the 0.45 mg tablets contain iron oxide black and iron oxide yellow; the 0.9 mg tablets also contain D&C yellow no. 10 aluminum lake, FD&C blue no. 1 aluminum lake and FD&C yellow no. 6 aluminum lake; and the 1.25 mg tablets contain iron oxide yellow.

CLINICAL PHARMACOLOGY

Endogenous estrogens are largely responsible for the development and maintenance of the female reproductive system and secondary sexual characteristics. Although circulating estrogens exist in a dynamic equilibrium of metabolic interconversions, estradiol is the principal intracellular human estrogen and is substantially more potent than its metabolites, estrone and estriol, at the receptor level.

The primary source of estrogen in normally cycling adult women is the ovarian follicle, which secretes 70 to 500 mcg of estradiol daily, depending on the phase of the menstrual cycle. After menopause, most endogenous estrogen is produced by conversion of androstenedione, secreted by the adrenal cortex, to estrone by peripheral tissues. Thus, estrone and the sulfate-conjugated form, estrone sulfate, are the most abundant circulating estrogens in postmenopausal women.

Estrogens act through binding to nuclear receptors in estrogen-responsive tissues. To date, two estrogen receptors have been identified. These vary in proportion from tissue to tissue.

Circulating estrogens modulate the pituitary secretion of the gonadotropins, luteinizing hormone (LH) and follicle-stimulating hormone (FSH), through a negative feedback mechanism. Estrogens act to reduce the elevated levels of these hormones in postmenopausal women.

A. Absorption

Synthetic conjugated estrogens, B are soluble in water and are well absorbed from the gastrointestinal tract after release from the drug formulation. ENJUVIA tablets release synthetic conjugated estrogens, B slowly over a period of several hours. Table 1 and Table 2 summarize the mean pharmacokinetic parameters for unconjugated (free) and conjugated (total) estrogens following single administration of two 0.625 mg tablets to 21 healthy postmenopausal women under fasting conditions. The effect of food on the bioavailability of synthetic conjugated estrogens, B following administration of ENJUVIA tablets has not been studied. However, the presence of food did not significantly affect the pharmacokinetics of a similar formulation of synthetic conjugated estrogens, B.

Table 1. Mean Pharmacokinetic Parameters of Unconjugated (Free) Estrogens Following a Single Dose of 2 x 0.625 mg ENJUVIA Tablets Under Fasting Conditions*
 | Cmax; (pg/mL) | tmax; (hr) | t1/2; (hr) | AUC0-48h; (pg●hr/mL)
Baseline-corrected estrone; (% CV) | 75.87; (39) | 9.29; (25) | 23.46; (59) | 1601.59; (41)
Equilin; (% CV) | 41.94; (49) | 8.38; (27) | 15.09; (55) | 707.21; (46)
Cmax = peak plasma concentration; tmax = time peak concentration occurs; t1/2 = apparent terminal-phase disposition half-life. AUC0-48h = total area under the concentration-time curve from time zero to time of last quantifiable concentration (48h) ; * Δ^8,9 Dehydroestrone (free) levels were below the assay limit of quantitation; CV= Coefficient of Variance

Table 2. Mean Pharmacokinetic Parameters of Conjugated (Total) Estrogens Following a Single Dose of 2 x 0.625 mg ENJUVIA Tablets Under Fasting Conditions
 | Cmax; (ng/mL) | tmax; (h) | t1/2; (h) | AUC0-48h; (ng●h/mL)
Baseline-corrected estrone; (% CV) | 3.74; (29) | 8.00; (27) | 14.26; (26) | 62.03; (34)
Equilin; (% CV) | 3.69; (44) | 8.05; (36) | 11.28; (28) | 58.25; (53)
Δ^8,9 Dehydroestrone; (%CV) | 0.74; (32) | 7.55; (37) | 14.14; (26) | 12.93; (39)
Cmax = peak plasma concentration; tmax = time peak concentration occurs; t1/2 = apparent terminal-phase disposition half-life; AUC0-48h = total area under the concentration-time curve from time zero to time of last quantifiable concentration (48h); CV= Coefficient of Variance

B. Distribution

The distribution of exogenous estrogens is similar to that of endogenous estrogens. Estrogens are widely distributed in the body and are generally found in higher concentrations in the sex hormone target organs. Estrogens circulate in the blood largely bound to sex hormone binding globulin (SHBG) and albumin.

C. Metabolism

Exogenous estrogens are metabolized in the same manner as endogenous estrogens. Circulating estrogens exist in a dynamic equilibrium of metabolic interconversions. These transformations take place mainly in the liver. Estradiol is converted reversibly to estrone, and both can be converted to estriol, which is the major urinary metabolite. Estrogens also undergo enterohepatic recirculation via sulfate and glucuronide conjugation in the liver, biliary secretion of conjugates into the intestine, and hydrolysis in the intestine followed by reabsorption. In postmenopausal women, a significant portion of the circulating estrogens exists as sulfate conjugates, especially estrone sulfate, which serves as a circulating reservoir for the formation of more active estrogens.

D. Excretion

Estradiol, estrone, and estriol are excreted in the urine along with glucuronide and sulfate conjugates. The mean (SD) apparent terminal elimination half-life (t½) of conjugated estrone is 14 (± 6) hours and conjugated equilin is 11 (± 6) hours.

E. Special Populations

No pharmacokinetic studies were conducted in special populations, including patients with renal or hepatic impairment.

F. Drug Interactions

In vitro and in vivo studies have shown that estrogens are metabolized partially by cytochrome P450 3A4 (CYP3A4). Therefore, inducers or inhibitors of CYP3A4 may affect estrogen drug metabolism. Inducers of CYP3A4, such as St. John’s Wort preparations (Hypericum perforatum), phenobarbital, carbamazepine, and rifampin, may reduce plasma concentrations of estrogens, possibly resulting in a decrease in therapeutic effects and/or changes in the uterine bleeding profile. Inhibitors of CYP3A4, such as erythromycin, clarithromycin, ketoconazole, itraconazole, ritonavir, and grapefruit juice, may increase plasma concentrations of estrogens and may result in side effects.

CLINICAL STUDIES

Effects on Vasomotor Symptoms

A randomized, double-blind, placebo-controlled, dose-ranging, multi-center clinical study was conducted to evaluate the safety and effectiveness of ENJUVIA tablets for the treatment of vasomotor symptoms in 281 naturally or surgically postmenopausal women aged 26 to 65 years who were experiencing a minimum of seven moderate to severe hot flushes per day or 50 per week at randomization. The majority (81%) of patients were Caucasian (n=228) and 17.4% were Black (n=49). Patients were randomized to receive ENJUVIA tablets 0.3 mg, 0.625 mg, 1.25 mg, or placebo once daily for 12 weeks.

ENJUVIA (0.3 mg, 0.625 mg and 1.25 mg tablets) was shown to be statistically better than placebo at weeks 4 and 12 for relief of both the frequency and severity of moderate to severe vasomotor symptoms (Table 3 and 4).

Table 3. Mean Number and Mean Change in Number of Moderate to Severe Hot Flushes Per Week ITT Population With LOCF
 | 0.3 mg; n=66 | 0.625 mg; n=71 | 1.25 mg; n=69 | Placebo; n=70
Baseline
Mean (SD) | 104.3 (57.7) | 97.3 (82.1) | 86.8 (42.1) | 96.4 (58.2)
Week 4
Mean (SD) | 47.0 (52.9) | 23.3 (26.9) | 24.6 (47.0) | 57.8 (47.5)
Mean Change from; Baseline (SE) | -49.8 (5.2) | -72.8 (5.0) | -68.3 (5.1) | -37.2 (5.0)
p-value versus placebo | 0.005 | <0.001 | <0.001 | ---
Week 12
Mean (SD) | 30.7 (47.7) | 12.2 (18.7) | 12.4 (26.3) | 47.5 (49.8)
Mean Change from; Baseline (SE) | -66.3 (4.6) | -84.6 (4.4) | -82.6 (4.5) | -48.3 (4.5)
p-value versus placebo | <0.001 | <0.001 | <0.001 | ---
ITT= Intent to treat; LOCF= Last Observation Carried Forward, SD= Standard Deviation; SE= Standard Error

Table 4. Mean Change in Severity of Moderate to Severe Hot Flushes Per Week, ITT Population with LOCF
 | 0.3 mg; n=66 | 0.625 mg; n=71 | 1.25 mg; n=69 | Placebo; n=70
Baseline
Mean (SD) | 2.5 (0.3) | 2.5 (0.3) | 2.5 (0.3) | 2.5 (0.3)
Week 4
Mean (SD) | 2.1 (0.8) | 1.9 (1.0) | 1.5 (1.1) | 2.2 (0.8)
Mean Change from; Baseline (SE) | -0.5 (0.1) | -0.6 (0.1) | -1.0 (0.1) | -0.3 (0.1)
p-value versus placebo | 0.036 | 0.002 | <0.001 | ---
Week 12
Mean (SD) | 1.5 (1.2) | 1.1 (1.2) | 1.0 (1.1) | 1.9 (1.1)
Mean Change from; Baseline (SE) | -1.0 (0.1) | -1.4 (0.1) | -1.5 (0.1) | -0.6 (0.1)
p-value versus placebo | 0.023 | <0.001 | <0.001 | ---
ITT= Intent to treat; LOCF= Last Observation Carried Forward, SD= Standard Deviation; SE= Standard Error

Effects on Vulvar and Vaginal Atrophy

A randomized, double-blind, placebo-controlled, multi-center clinical study was conducted to evaluate the safety and effectiveness of ENJUVIA 0.3 mg tablets for the treatment of symptoms of vulvar and vaginal atrophy in 248 naturally or surgically postmenopausal women between 32 to 81 years of age (mean 58.6 years) who at baseline had ≤ 5% superficial cells on a vaginal smear, a vaginal pH > 5.0, and who identified their most bothersome moderate to severe symptom of vulvar and vaginal atrophy. The majority (82%) of the women were Caucasian (n=203), 11% were Hispanic (n=26), 4% were Black (n=9) and 3% were Asian (n=6). All patients were assessed for improvement in the mean change from baseline to Week 12 for three co-primary efficacy variables: most bothersome symptom of vulvar and vaginal atrophy (defined as the moderate to severe symptom that had been identified by the patient as most bothersome to her at baseline); percentage of vaginal superficial cells and percentage of vaginal parabasal cells; and vaginal pH.

In this study, a statistically significant mean change between baseline and week 12 for the group treated with ENJUVIA 0.3 mg tablets compared to placebo was observed for the symptoms, vaginal dryness and pain with intercourse. See Table 5. ENJUVIA 0.3 mg tablets increased superficial cells by a mean of 17.1% as compared to 2.0% for placebo (statistically significant). A corresponding statistically significant mean reduction from baseline in parabasal cells (41.7% for ENJUVIA 0.3 mg tablets and 6.8% for placebo) was observed at week 12. The mean reduction between baseline and week 12 in the pH was 1.69 in the ENJUVIA 0.3 mg tablets group and 0.45 in the placebo group (statistically significant).

Table 5. Change from Baseline to Week 12 in the Severity of Vaginal Dryness and Pain with Intercourse, Symptoms That Were Identified by the Menopausal Study Patient as Her Most Bothersome Symptom of Vulvar and Vaginal Atrophy at Baseline
Most Bothersome Symptom at Baseline* | ENJUVIA 0.3 mg | Placebo
Vaginal Dryness
n | 56 | 54
Baseline Severity | 2.52 | 2.54
Mean Severity at Week 12 | 0.80 | 1.81
Mean Change in Severity from Baseline (s.d.) | -1.71 (0.85) | -0.72 (0.66)
p-value vs. placebo | <0.001 | ---
Pain With Intercourse
n | 35 | 40
Baseline Severity | 2.74 | 2.70
Mean Severity at Week 12 | 0.94 | 1.95
Mean Change in Severity from Baseline (s.d.) | -1.80 (1.02) | -0.75 (0.95)
p-value vs. placebo | <0.001 | ---
* Treatment differences assessed by ANCOVA or rank ANCOVA (% cell data) with baseline as covariate for the modified intent-to-treat population, last-observation-carried-forward data set.

Women’s Health Initiative Studies

The WHI enrolled approximately 27,000 predominantly healthy postmenopausal women in two substudies to assess the risks and benefits of either the use of oral conjugated estrogens (CE 0.625 mg) alone per day or in combination with medroxyprogesterone acetate (CE 0.625 mg/MPA 2.5 mg) per day compared to placebo in the prevention of certain chronic diseases. The primary endpoint was the incidence of coronary heart disease (CHD) (nonfatal myocardial infarction (MI), silent MI and CHD death), with invasive breast cancer as the primary adverse outcome studied. A “global index” included the earliest occurrence of CHD, invasive breast cancer, stroke, pulmonary embolism (PE), endometrial cancer (only in the estrogen plus progestin substudy), colorectal cancer, hip fracture, or death due to other causes. The study did not evaluate the effects of CE or CE/MPA on menopausal symptoms.

The estrogen-alone substudy was stopped early because an increased risk of stroke was observed and it was deemed that no further information would be obtained regarding the risks and benefits of estrogen alone in predetermined primary endpoints. Results of the estrogen-alone substudy, which included 10,739 women (average age of 63 years, range 50 to 79; 75.3% White, 15.1% Black, 6.1% Hispanic, 3.6% Other), after an average follow-up of 6.8 years are presented in Table 6.

Table 6: Relative And Absolute Risk Seen In The Estrogen-Alone Substudy Of WHI [Nominal confidence intervals unadjusted for multiple looks and multiple comparisons]
Event | Relative Risk CE vs. Placebo (95% nCI) | Placebo n = 5,429 | CE n = 5,310
Event | Relative Risk CE vs. Placebo (95% nCI) | Absolute Risk per 10,000 Women-Years
CHD events [Results are based on centrally adjudicated data for an average follow-up of 7.1 years] Nonfatal MI CHD death | 0.95 (0.79- 1.16) 0.91 (0.73-1.14) 1.01(0.71- 1.43) | 56 43 16 | 53 40 16
Stroke [Results are based on an average follow-up of 6.8 years] | 1.39 (1.10-1.77) | 32 | 44
Deep vein thrombosis, [Not included in Global Index] | 1.47 (1.06-2.06) | 15 | 23
Pulmonary embolism | 1.37 (0.90-2.07) | 10 | 14
Invasive breast cancer | 0.80 (0.62-1.04) | 34 | 28
Colorectal cancer | 1.08 (0.75-1.55) | 16 | 17
Hip fracture | 0.61 (0.41-0.91) | 17 | 11
Vertebral fractures, | 0.62 (0.42-0.93) | 17 | 11
Total fractures, | 0.70 (0.63-0.79) | 195 | 139
Death due to other causes, | 1.08 (0.88-1.32) | 50 | 53
Overall mortality, | 1.04 (0.88-1.32) | 78 | 81
Global index, | 1.01 (0.91-1.12) | 190 | 192

For those outcomes included in the WHI “global index” that reached statistical significance, the absolute excess risk per 10,000 women-years in the group treated with estrogen-alone was 12 more strokes, while the absolute risk reduction per 10,000 women-years was 6 fewer hip fractures. The absolute excess risk of events included in the “global index” was a nonsignificant 2 events per 10,000 women-years. There was no difference between the groups in terms of all-cause mortality. (See BOXED WARNINGS, WARNINGS, and PRECAUTIONS.)

Final centrally adjudicated results for CHD events and centrally adjudicated results for invasive breast cancer incidence from the estrogen-alone substudy, after an average follow-up of 7.1 years, reported no overall difference for primary CHD events (nonfatal MI, silent MI and CHD death) and invasive breast cancer incidence in women receiving CE alone compared with placebo (see Table 6).

The estrogen-plus-progestin substudy was also stopped early because, according to the predefined stopping rule, after an average follow-up of 5.2 years of treatment, the increased risk of breast cancer and cardiovascular events exceeded the specified benefits included in the “global index.” The absolute excess risk of events included in the “global index” was 19 per 10,000 women-years (RR 1.15, 95% nCI 1.03-1.28).

For those outcomes included in the WHI “global index” that reached statistical significance after 5.6 years of follow-up, the absolute excess risks per 10,000 women-years in the group treated with CE/MPA were 6 more CHD events, 7 more strokes, 10 more PEs, and 8 more invasive breast cancers, while the absolute risk reductions per 10,000 women-years were 7 fewer colorectal cancers and 5 fewer hip fractures. (See BOXED WARNINGS, WARNINGS, and PRECAUTIONS.)

Results of the estrogen-plus-progestin substudy, which included 16,608 women (average age of 63 years, range 50 to 79; 83.9% White, 6.8% Black, 5.4% Hispanic, 3.9% Other) are presented in Table 7 below.

Table 7. Relative And Absolute Risk Seen in the Estrogen-Plus Progestin Substudy of WHI at an Average of 5.6 Years
Event | Relative Risk CE/MPA vs. Placebo (95% nCI) | Placebo n = 8102 | CE/MPA n = 8506
Event | Relative Risk CE/MPA vs. Placebo (95% nCI) | Absolute Risk per 10,000 Women-Years
CHD events Non-fatal MI CHD death | 1.24 (1.00-1.54) 1.28 (1.00-1.63) 1.10 (0.70-1.75) | 33 25 8 | 39 31 8
All strokes | 1.31 (1.02-1.68) | 24 | 31
Ischemic stroke | 1.44 (1.09 -1.90) | 18 | 26
Deep vein thrombosis | 1.95 (1.43 – 2.67) | 13 | 26
Pulmonary embolism | 2.13 (1.45-3.11) | 8 | 18
Invasive breast cancer | 1.24 (1.01-1.54) | 3 | 41
Invasive colorectal cancer | 0.56 (0.38-0.81) | 16 | 9
Endometrial cancer | 0.81 (0.48-1.36) | 7 | 6
Cervical cancer | 1.44 (0.47-4.42) | 1 | 2
Hip fracture | 0.67 (0.47-0.96) | 16 | 11
Vertebral fractures | 0.65 (0.46-0.92) | 17 | 11
Lower arm/wrist fractures | 0.71 (0.59-0.85) | 62 | 44
Total fractures | 0.76 (0.69-0.83) | 199 | 152

Women’s Health Initiative Memory Study

The estrogen-alone Women’s Health Initiative Memory Study (WHIMS), a substudy of WHI study, enrolled 2,947 predominantly healthy postmenopausal women 65 years of age and older (45% were age 65 to 69 years, 36% were 70 to 74 years, and 19% were 75 years of age and older) to evaluate the effects of conjugated estrogens (CE 0.625 mg) on the incidence of probable dementia (primary outcome) compared with placebo.

After an average follow-up of 5.2 years, 28 women in the estrogen-alone group (37 per 10,000 women-years) and 19 in the placebo group (25 per 10,000 women-years) were diagnosed with probable dementia. The relative risk of probable dementia in the estrogen-alone group was 1.49 (95% CI 0.83-2.66) compared to placebo. It is unknown whether these findings apply to younger postmenopausal women. (See BOXED WARNINGS, WARNINGS, Dementia and PRECAUTIONS, Geriatric Use.)

The estrogen-plus-progestin WHIMS substudy enrolled 4,532 predominantly healthy postmenopausal women 65 years of age and older (47% were aged 65 to 69 years, 35% were 70 to 74 years, and 18% were 75 years of age and older) to evaluate the effects of CE 0.625 mg plus MPA 2.5 mg on the incidence of probable dementia (primary outcome) compared with placebo.

After an average follow-up of 4 years, 40 women in the estrogen plus progestin group (45 per 10,000 women-years) and 21 in the placebo group (22 per 10,000 women-years) were diagnosed with probable dementia. The relative risk of probable dementia in the hormone therapy group was 2.05 (95% CI 1.21-3.48) compared to placebo. Differences between groups became apparent in the first year of treatment. It is unknown whether these findings apply to younger postmenopausal women. (See BOXED WARNING, WARNINGS, Dementia, and PRECAUTIONS, Geriatric Use.)

When data from the two populations were pooled as planned in the WHIMS protocol, the reported overall relative risk for probable dementia was 1.76 (95% CI 1.19-2.60). It is unknown whether these findings apply to younger postmenopausal women. (See BOXED WARNING, WARNINGS, Dementia, and PRECAUTIONS, Geriatric Use.)

INDICATIONS AND USAGE

ENJUVIA tablets are indicated in the:

1. Treatment of moderate to severe vasomotor symptoms associated with menopause.
2. Treatment of moderate to severe vaginal dryness and pain with intercourse, symptoms of vulvar and vaginal atrophy, associated with menopause. When prescribing solely for the treatment of moderate to severe vaginal dryness and pain with intercourse, topical vaginal products should be considered.

CONTRAINDICATIONS

ENJUVIA tablets should not be used in women with any of the following conditions:

1. Undiagnosed abnormal genital bleeding.
2. Known, suspected, or history of cancer of the breast.
3. Known or suspected estrogen-dependent neoplasia.
4. Active deep vein thrombosis, pulmonary embolism or a history of these conditions.
5. Active or recent (e.g., within the past year) arterial thromboembolic disease (e.g., stroke, myocardial infarction).
6. Liver dysfunction or disease.
7. Known hypersensitivity to the ingredients of ENJUVIA Tablets.
8. Known or suspected pregnancy. There is no indication for ENJUVIA in pregnancy. There appears to be little or no increased risk of birth defects in children born to women who have used estrogens and progestins from oral contraceptives inadvertently during early pregnancy. (See PRECAUTIONS.)

WARNINGS

See BOXED WARNINGS.

1. Cardiovascular disorders

Estrogen and estrogen/progestin therapies have been associated with an increased risk of cardiovascular events such as myocardial infarction and stroke, as well as venous thrombosis and pulmonary embolism (venous thromboembolism (VTE)). Should any of these occur or be suspected, estrogens should be discontinued immediately.

Risk factors for arterial vascular disease (e.g., hypertension, diabetes mellitus, tobacco use, hypercholesterolemia, and obesity) and/or venous thromboembolism (e.g., personal history or family history of VTE, obesity, and systemic lupus erythematosus) should be managed appropriately.

a. Stroke
  In the estrogen-alone substudy of the Women’s Health Initiative (WHI) study, statistically significant increased risk of stroke was reported in women receiving CE 0.625 mg daily compared to women receiving placebo (44 versus 32 per 10,000 women-years). The increase in risk was demonstrated in year 1 and persisted. (See CLINICAL STUDIES).
  In the estrogen-plus-progestin substudy of WHI study, a statistically significant increased risk of stroke was reported in women receiving CE/MPA 0.625 mg/2.5 mg daily compared to women receiving placebo (31 vs. 24 per 10, 000 women-years). The increase in risk was demonstrated after the first year and persisted. (See CLINICAL PHARMACOLOGY, CLINICAL STUDIES.)
b. Coronary heart disease
  In the estrogen-alone substudy of WHI, no overall effect on coronary heart disease (CHD) events (defined as non-fatal MI, silent MI or death due to CHD) was reported in women receiving estrogen alone compared to placebo. (See CLINICAL STUDIES.)
  In the estrogen-plus-progestin substudy of the WHI study, no statistically significant increase of CHD events was reported in women receiving CE/MPA compared to women receiving placebo (39 versus 33 per 10,000 women-years). An increase in relative risk was demonstrated in year 1, and a trend toward decreasing relative risk was reported in years 2 through 5.
  In postmenopausal women with documented heart disease (n = 2,763, average age 66.7 years), a controlled clinical trial of secondary prevention of cardiovascular disease (Heart and Estrogen/Progestin Replacement Study (HERS)) treatment with CE/MPA (0.625 mg/2.5 mg per day) demonstrated no cardiovascular benefit. During an average follow-up of 4.1 years, treatment with CE/MPA did not reduce the overall rate of CHD events in postmenopausal women with established coronary heart disease. There were more CHD events in the CE/MPA-treated group than in the placebo group in year 1, but not during the subsequent years. Participation in an open label extension of the original HERS trial (HERS II) was agreed to by 2,321 women. Average follow-up in HERS II was an additional 2.7 years, for a total of 6.8 years overall. Rates of CHD events were comparable among women in the CE/MPA group and the placebo group in HERS, HERS II, and overall.
  Large doses of estrogen (5 mg conjugated estrogens per day), comparable to those used to treat cancer of the prostate and breast, have been shown in a large prospective clinical trial in men to increase the risks of nonfatal myocardial infarction, pulmonary embolism, and thrombophlebitis.
c. Venous thromboembolism
  In the estrogen-alone substudy of WHI the risk of VTE (DVT and pulmonary embolism [PE]), was reported to be increased for women taking conjugated equine estrogens (30 vs. 22 per 10,000 women-years), although only the increased risk of DVT reached statistical significance (23 vs. 15 per 10,000 women years). The increase in VTE risk was demonstrated during the first year. (See CLINICAL STUDIES.)
  In the estrogen-plus-progestin substudy of WHI, a statistically significant 2-fold greater rate of VTE was reported in women receiving CE/MPA compared to women receiving placebo (35 vs. 17 per 10,000 women-years). Statistically significant increases in risk for both DVT (26 vs. 13 per 10,000 women-years) and PE (18 vs. 8 per 10,000 women-years) were also demonstrated. The increase in VTE risk was demonstrated during the first year and persisted.
  If feasible, estrogens should be discontinued at least 4 to 6 weeks before surgery of the type associated with an increased risk of thromboembolism, or during periods of prolonged immobilization.

2. Malignant neoplasms

a. Endometrial cancer
  The use of unopposed estrogens in women with intact uteri has been associated with an increased risk of endometrial cancer. The reported endometrial cancer risk among unopposed estrogen users is about 2- to 12-times greater than in non- users, and appears dependent on duration of treatment and on estrogen dose. Most studies show no significant increased risk associated with use of estrogens for less than 1 year. The greatest risk appears associated with prolonged use, with increased risks of 15- to 24-fold for 5 to 10 years or more. This risk has been shown to persist for at least 8 to 15 years after estrogen therapy is discontinued.
  Clinical surveillance of all women taking estrogen/progestin combinations is important. Adequate diagnostic measures, including endometrial sampling when indicated, should be undertaken to rule out malignancy in all cases of undiagnosed persistent or recurring abnormal vaginal bleeding. There is no evidence that the use of natural estrogens results in a different endometrial risk profile than synthetic estrogens of equivalent estrogen dose. Adding a progestin to estrogen therapy has been shown to reduce the risk of endometrial hyperplasia, which may be a precursor to endometrial cancer.
b. Breast cancer
  In some studies, the use of estrogens and progestins by postmenopausal women has been reported to increase the risk of breast cancer. The most important randomized clinical trial providing information about this issue is the Women's Health Initiative (WHI) (see CLINICAL STUDIES). The results from observational studies are generally consistent with those of the WHI clinical trial.
  Observational studies have also reported an increased risk of breast cancer for estrogen-plus-progestin combination therapy, and a smaller increased risk for estrogen-alone therapy, after several years of use. For both findings, the excess risk increased with duration of use, and appeared to return to baseline over about five years after stopping treatment (only the observational studies have substantial data on risk after stopping). In these studies, the risk of breast cancer was greater, and became apparent earlier, with estrogen-plus-progestin combination therapy as compared to estrogen-alone therapy. However, these studies have not found significant variation in the risk of breast cancer among different estrogens or among different estrogen-plus-progestin combinations, doses, or routes of administration.
  In the estrogen-alone substudy of WHI, after an average of 7.1 years of follow-up, CE (0.625 mg daily) was not associated with an increased risk of invasive breast cancer (RR 0.80, 95% nCI 0.62-1.04).
  In the estrogen-plus-progestin substudy, after a mean follow-up of 5.6 years, the WHI substudy reported an increased risk of breast cancer. In this substudy, prior use of estrogen alone or estrogen-plus-progestin combination hormone therapy was reported by 26% of the women. The relative risk of invasive breast cancer was 1.24 (95% nCI 1.01-1.54), and the absolute risk was 41 vs. 33 cases per 10,000 women-years, for estrogen plus progestin compared with placebo, respectively. Among women who reported prior use of hormone therapy, the relative risk of invasive breast cancer was 1.86, and the absolute risk was 46 vs. 25 cases per 10,000 women-years, for estrogen plus progestin compared with placebo. Among women who reported no prior use of hormone therapy, the relative risk of invasive breast cancer was 1.09, and the absolute risk was 40 vs. 36 cases per 10,000 women-years for estrogen plus progestin compared with placebo. In the WHI trial, invasive breast cancers were larger and diagnosed at a more advanced stage in the estrogen-plus-progestin group compared with the placebo group. Metastatic disease was rare, with no apparent difference between the two groups. Other prognostic factors, such as histologic subtype, grade and hormone receptor status did not differ between the groups.
  The use of estrogen alone and estrogen plus progestin has been reported to result in an increase in abnormal mammograms requiring further evaluation.
  All women should receive yearly breast examinations by a healthcare provider and perform monthly breast self-examinations. In addition, mammography examinations should be scheduled based on patient age, risk factors, and prior mammogram results.

3. Dementia

In the estrogen-alone Women's Health Initiative Memory Study (WHIMS), a substudy of WHI, a population of 2,947 hysterectomized women aged 65 to 79 years was randomized to CE (0.625 mg daily) or placebo. In the estrogen-plus-progestin WHIMS substudy, a population of 4,532 postmenopausal women aged 65 to 79 years was randomized to CE/MPA (0.625 mg/2.5 mg daily) or placebo.

In the estrogen-alone substudy, after an average follow-up of 5.2 years, 28 women in the estrogen-alone group and 19 women in the placebo group were diagnosed with probable dementia. The relative risk of probable dementia for CE alone vs. placebo was 1.49 (95% CI 0.83-2.66). The absolute risk of probable dementia for CE alone vs. placebo was 37 vs. 25 cases per 10,000 women-years.

In the estrogen-plus-progestin substudy, after an average follow-up of four years, 40 women in the estrogen-plus-progestin group and 21 women in the placebo group were diagnosed with probable dementia. The relative risk of probable dementia for estrogen plus progestin vs. placebo was 2.05 (95% CI 1.21-3.48). The absolute risk of probable dementia for CE/MPA vs. placebo was 45 vs. 22 cases per 10,000 women-years.

When data from the two populations were pooled as planned in the WHIMS protocol, the reported overall relative risk for probable dementia was 1.76 (95% CI 1.19-2.60). Since both substudies were conducted in women aged 65 to 79 years, it is unknown whether these findings apply to younger postmenopausal women. (See BOXED WARNINGS and PRECAUTIONS, and Geriatric Use.)

4. Gallbladder disease

A two- to four-fold increase in the risk of gallbladder disease requiring surgery in postmenopausal women receiving estrogens has been reported.

5. Hypercalcemia

Estrogen administration may lead to severe hypercalcemia in patients with breast cancer and bone metastases. If hypercalcemia occurs, use of the drug should be stopped and appropriate measures taken to reduce the serum calcium level.

6. Visual abnormalities

Retinal vascular thrombosis has been reported in patients receiving estrogens. Discontinue medication pending examination if there is sudden partial or complete loss of vision, or a sudden onset of proptosis, diplopia, or migraine. If examination reveals papilledema or retinal vascular lesions, estrogens should be permanently discontinued.

PRECAUTIONS

A. General

1. Addition of a progestin when a woman has not had a hysterectomy
  Studies of the addition of a progestin for 10 or more days of a cycle of estrogen administration, or daily with estrogen in a continuous regimen, have reported a lowered incidence of endometrial hyperplasia than would be induced by estrogen treatment alone. Endometrial hyperplasia may be a precursor to endometrial cancer.
  There are, however, possible risks that may be associated with the use of progestins with estrogens compared to estrogen-alone regimens. These include: a possible increased risk of breast cancer, adverse effects on lipoprotein metabolism (e.g., lowering HDL, raising LDL) and impairment of glucose tolerance.
2. Elevated blood pressure
  In a small number of case reports, substantial increases in blood pressure have been attributed to idiosyncratic reactions to estrogens. In a large, randomized, placebo-controlled clinical trial, a generalized effect of estrogens on blood pressure was not seen. Blood pressure should be monitored at regular intervals with estrogen use.
3. Hypertriglyceridemia
  In patients with pre-existing hypertriglyceridemia, estrogen therapy may be associated with elevations of plasma triglycerides leading to pancreatitis and other complications.
4. Impaired liver function and past history of cholestatic jaundice
  Estrogens may be poorly metabolized in patients with impaired liver function. For patients with a history of cholestatic jaundice associated with past estrogen use or with pregnancy, caution should be exercised and in the case of recurrence, medication should be discontinued.
5. Hypothyroidism
  Estrogen administration leads to increased thyroid-binding globulin (TBG) levels. Patients with normal thyroid function can compensate for the increased TBG by making more thyroid hormone, thus maintaining free T4 and T3 serum concentrations in the normal range. Patients dependent on thyroid hormone replacement therapy who are also receiving estrogens may require increased doses of their thyroid replacement therapy. These patients should have their thyroid function monitored to maintain their free thyroid hormone levels in an acceptable range.
6. Fluid retention
  Estrogens may cause some degree of fluid retention. Because of this, patients who have conditions that might be influenced by this factor, such as a cardiac or renal dysfunction, warrant careful observation when estrogens are prescribed.
7. Hypocalcemia
  Estrogens should be used with caution in individuals with severe hypocalcemia.
8. Ovarian cancer
  The estrogen-plus-progestin substudy of WHI reported that after an average follow-up of 5.6 years, the relative risk for ovarian cancer for estrogen plus progestin vs. placebo was 1.58 (95% nCI 0.77 – 3.24), but was not statistically significant. The absolute risk for estrogen plus progestin vs. placebo was 4.2 vs. 2.7 cases per 10,000 women-years. In some epidemiologic studies, the use of estrogen only products, in particular for 10 or more years, has been associated with an increased risk of ovarian cancer. Other epidemiologic studies have not found these associations.
9. Exacerbation of other endometriosis
  Endometriosis may be exacerbated with administration of estrogens. Malignant transformation of residual endometrial implants has been reported in women treated post-hysterectomy with estrogen-alone therapy. For patients known to have residual endometriosis post-hysterectomy, the addition of progestin should be considered.
10. Exacerbation of other conditions
  Estrogens may cause an exacerbation of asthma, diabetes mellitus, epilepsy, migraine, porphyria, systemic lupus erythematosus, and hepatic hemangiomas and should be used with caution in women with these conditions.

B. Information for Patients

Physicians are advised to discuss the PATIENT INFORMATION leaflet with patients for whom they prescribe ENJUVIA tablets.

C. Laboratory Tests

Estrogen administration should be initiated at the lowest dose approved for the indication and then guided by clinical response rather than by serum hormone levels (e.g., estradiol, FSH).

D. Drug/Laboratory Test Interactions

1. Accelerated prothrombin time, partial thromboplastin time, and platelet aggregation time; increased platelet count; increased factors II, VII antigen, VIII antigen, VIII coagulant activity, IX, X, XII, VII-X complex, II-VII-X complex, and beta-thromboglobulin; decreased levels of anti-factor Xa and antithrombin III, decreased antithrombin III activity; increased levels of fibrinogen and fibrinogen activity; increased plasminogen antigen and activity.
2. Increased thyroid-binding globulin (TBG) levels leading to increased circulating total thyroid hormone levels as measured by protein-bound iodine (PBI), T4 levels (by column or by radioimmunoassay) or T3 levels by radioimmunoassay. T3 resin uptake is decreased, reflecting the elevated TBG. Free T4 and free T3 concentrations are unaltered. Patients on thyroid replacement therapy may require higher doses of thyroid hormone.
3. Other binding proteins may be elevated in serum, (i.e., corticosteroid binding globulin (CBG), sex hormone binding globulin (SHBG)) leading to increased total circulating corticosteroids and sex steroids, respectively. Free hormone concentrations may be decreased. Other plasma proteins may be increased (angiotensinogen/renin substrate, alpha-1-antitrypsin, ceruloplasmin).
4. Increased plasma HDL and HDL2 cholesterol subfraction concentrations, reduced LDL cholesterol concentration, increased triglyceride levels.
5. Impaired glucose tolerance.
6. Reduced response to metyrapone test.

E. Carcinogenesis, Mutagenesis, Impairment of Fertility

See BOXED WARNINGS, WARNINGS and PRECAUTIONS.

Long-term continuous administration of natural and synthetic estrogens in certain animal species increases the frequency of carcinomas of the breast, uterus, cervix, vagina, testis, and liver.

F. Pregnancy

ENJUVIA tablets should not be used during pregnancy. (See CONTRAINDICATIONS.)

G. Nursing Mothers

Estrogen administration to nursing mothers has been shown to decrease the quantity and quality of the milk. Detectable amounts of estrogens have been identified in the milk of mothers receiving this drug. Caution should be exercised when ENJUVIA is administered to a nursing woman.

H. Pediatric Use

The safety and efficacy of ENJUVIA tablets in pediatric patients has not been established.

I. Geriatric Use

Clinical studies of ENJUVIA did not include sufficient numbers of subjects aged 65 and over to determine whether they respond differently from younger subjects.

Of the total number of subjects in the estrogen-alone substudy of the WHI study, 46 percent (n = 4,943) were 65 years and older, while 7.1 percent (n = 767) were 75 years and older. There was a higher relative risk (CE versus placebo) of stroke in women less than 75 years of age compared to women 75 years and over.

In the estrogen-alone substudy of WHIMS, a substudy of WHI, a population of 2,947 hysterectomized women, aged 65 to 79 years, was randomized to CE (0.625 per day) or placebo. After an average follow-up of 5.2 years, the relative risk (CE vs. placebo) of probable dementia was 1.49 (95% CI 0.83-2.66). The absolute risk of developing probable dementia with estrogen alone was 37 vs. 25 cases per 10,000 women-years with placebo.

Of the total number of subjects in the estrogen-plus-progestin substudy of the WHI study, 44 percent (n = 7,320) were 65-74 years of age, while 6.6 percent (n = 1,095) were 75 years and older. There was a higher relative risk (CE/MPA versus placebo) of non-fatal stroke and invasive breast cancer in women 75 and older compared to women less than 75 years of age. In women greater than 75, the increased risk of non-fatal stroke and invasive breast cancer observed in the estrogen-plus-progestin combination group compared to the placebo group was 75 vs. 24 per 10,000 women-years and 52 vs. 12 per 10,000 women-years, respectively.

In the estrogen-plus-progestin substudy of WHIMS, a population of 4,532 postmenopausal women, aged 65 to 79 years, was randomized to CE/MPA (CE 0.625 mg/2.5 mg). In the estrogen-plus-progestin group, after an average follow-up of 4 years, the relative risk (CE/MPA versus placebo) of probable dementia was 2.05 (95% CI 1.21-3.48). The absolute risk of developing probable dementia with CE/MPA was 45 vs. 22 cases per 10,000 women-years with placebo.

Seventy-nine percent of the cases of probable dementia occurred in women that were older than 70 for the CE group, and 82 percent of the cases of probable dementia occurred in women who were older than 70 in the CE/MPA group. The most common classification of probable dementia in both the treatment groups and placebo groups was Alzheimer’s disease.

When data from the two populations were pooled as planned in the WHIMS protocol, the reported overall relative risk for probable dementia was 1.76 (95% CI 1.19-2.60). Since both substudies were conducted in women aged 65 to 79 years, it is unknown whether these findings apply to younger postmenopausal women. (See BOXED WARNINGS and WARNINGS, Dementia.)

ADVERSE REACTIONS

See BOXED WARNINGS, WARNINGS and PRECAUTIONS.

Because clinical trials are conducted under widely varying conditions, adverse reaction rates observed in the clinical trials of a drug cannot be directly compared to rates in the clinical trials of another drug and may not reflect the rates observed in practice. The adverse reaction information from clinical trials does, however, provide a basis for identifying the adverse events that appear to be related to drug use and for approximating rates.

In a 12-week clinical trial, 209 postmenopausal women with vasomotor symptoms were treated with ENJUVIA. Adverse events that occurred in the study at a rate greater than or equal to 5% and greater than placebo, regardless of relationship to study drug, are summarized in Table 8.

Table 8. ENJUVIA Tablets – Number (%) of Patients Reporting Aderse Events* with ≥ 5% Occurrence Rate by Body System
Body System/Adverse Event* | 0.3 mg; n=68 | 0.625 mg; n=72 | 1.25 mg; n=69 | Placebo; n=72
Number of Patients in Safety Sample (%) | 68 (100) | 72 (100) | 69 (100) | 72 (100)
Number of Patients with Adverse Events (%) | 49 (72) | 55 (76) | 56 (81) | 51 (71)
Number of Patients without Adverse Events (%) | 19 (28) | 17 (24) | 13 (19) | 21 (29)
Body as a Whole
Abdominal Pain | 3 (4) | 11 (15) | 3 (4) | 7 (10)
Accidental Injury | 6 (8) | 2 (3) | 3 (4) | 5 (7)
Flu Syndrome | 4 (6) | 3 (4) | 5 (7) | 3 (4)
Headache | 10 (15) | 18 (25) | 11 (16) | 15 (21)
Pain | 10 (15) | 14 (19) | 7 (10) | 6 (8)
Digestive System
Flatulence | 3 (4) | 5 (7) | 3 (4) | 2 (3)
Nausea | 5 (7) | 7 (10) | 8 (12) | 6 (8)
Nervous System
Dizziness | 5 (7) | 3 (4) | 1 (1) | 3 (4)
Paresthesia | 0 | 4 (6) | 1 (1) | 0
Respiratory System
Bronchitis | 0 | 3 (4) | 5 (7) | 3 (4)
Rhinitis | 3 (4) | 4 (6) | 5 (7) | 4 (6)
Sinusitis | 2 (3) | 3 (4) | 5 (7) | 2 (3)
Urogenital System
Breast Pain | 0 | 9 (12) | 10 (14) | 3 (4)
Dysmenorrhea | 1 (2) | 6 (8) | 1 (1) | 2 (3)
Vaginitis | 1 (2) | 5 (7) | 2 (3) | 3 (4)
*Treatment-emergent adverse events, regardless of relationship to study drug

In a second 12-week clinical trial, 310 women with symptoms of vulvar and vaginal atrophy were treated (154 women with ENJUVIA 0.3 mg tablets and 156 women with placebo). The only adverse event that occurred at a rate of >5% was headache; seven patients (4.55%) with ENJUVIA and twelve patients (7.69%) with placebo.

The following additional adverse reactions have been reported with estrogen and/or progestin therapy:

1. Genitourinary system
  Changes in vaginal bleeding pattern and abnormal withdrawal bleeding or flow; breakthrough bleeding; spotting; dysmenorrhea; increase in size of uterine leiomyomata; vaginitis, including vaginal candidiasis; change in amount of cervical secretion; changes in cervical ectropion; ovarian cancer; endometrial hyperplasia; endometrial cancer.
2. Breasts
  Tenderness, enlargement, pain, nipple discharge, galactorrhea; fibrocystic breast changes; breast cancer.
3. Cardiovascular
  Deep and superficial venous thrombosis; pulmonary embolism; thrombophlebitis; myocardial infarction; stroke; increase in blood pressure.
4. Gastrointestinal
  Nausea, vomiting; abdominal cramps, bloating; cholestatic jaundice; increased incidence of gallbladder disease; pancreatitis, enlargement of hepatic hemangiomas.
5. Skin
  Chloasma or melasma that may persist when drug is discontinued; erythema multiforme; erythema nodosum; hemorrhagic eruption; loss of scalp hair; hirsutism; pruritus, rash.
6. Eyes
  Retinal vascular thrombosis, intolerance to contact lenses.
7. Central Nervous System
  Headache; migraine; dizziness; mental depression; chorea; nervousness; mood disturbances; irritability; exacerbation of epilepsy, dementia.
8. Miscellaneous
  Increase or decrease in weight; reduced carbohydrate tolerance; aggravation of porphyria; edema; arthralgias; leg cramps; changes in libido; urticaria, angioedema, anaphylactoid/anaphylactic reactions; hypocalcemia; exacerbation of asthma; increased triglycerides.

OVERDOSAGE

Serious ill effects have not been reported following acute ingestion of large doses of estrogen-containing products by young children. Overdosage of estrogen may cause nausea and vomiting, and withdrawal bleeding may occur in females.

DOSAGE AND ADMINISTRATION

When estrogen is prescribed for a postmenopausal woman with a uterus, a progestin should also be initiated to reduce the risk of endometrial cancer. A woman without a uterus does not need progestin. Use of estrogen, alone or in combination with a progestin, should be with the lowest effective dose and for the shortest duration consistent with treatment goals and risks for the individual woman. Patients should be re-evaluated periodically as clinically appropriate (e.g., 3-month to 6-month intervals) to determine if treatment is still necessary (see BOXED WARNINGS and WARNINGS). For women who have a uterus, adequate diagnostic measures, such as endometrial sampling, when indicated, should be undertaken to rule out malignancy in cases of undiagnosed persistent or recurring abnormal vaginal bleeding.

ENJUVIA tablets are taken orally, once daily for:

1. The treatment of moderate to severe vasomotor symptoms, associated with menopause.
  - ENJUVIA 0.3 mg
  - ENJUVIA 0.45 mg
  - ENJUVIA 0.625 mg
  - ENJUVIA 0.9 mg
  - ENJUVIA 1.25 mg
2. The treatment of moderate to severe vaginal dryness and pain with intercourse, symptoms of vulvar and vaginal atrophy, associated with menopause. When prescribing solely for the treatment of moderate to severe vaginal dryness and pain during intercourse, topical vaginal products should be considered.
  - ENJUVIA 0.3 mg

Patients should be started at the lowest approved dose of 0.3 mg ENJUVIA daily. Subsequent dosage adjustment (which will differ depending on the indication) may be made based upon the individual patient response. This dose should be periodically reassessed by the healthcare provider.

HOW SUPPLIED

ENJUVIA®

(synthetic conjugated estrogens, B) Tablets

0.3 mg:

The tablets are oval, white, film-coated, and debossed with “E” on one side and “1” on the reverse and are available in bottles of:

10 Tablets | NDC 54868-6164-0
30 Tablets | NDC 54868-6164-1

0.625 mg:

The tablets are oval, pink, film-coated, and debossed with “E” on one side and “3” on the reverse and are available in bottles of:

10 Tablets | NDC 54868-6163-0
30 Tablets | NDC 54868-6163-1

0.9 mg:

The tablets are oval, light blue-green, film-coated, and debossed with “E” on one side and “5” on the reverse and are available in bottles of:

10 Tablets | NDC 54868-6165-0
30 Tablets | NDC 54868-6165-1

Store at 20° to 25°C (68° to 77°F) [See USP Controlled Room Temperature].

Keep this and all drugs out of the reach of children.
Dispense in a tight container with a child-resistant closure.
Pharmacist: Include one “Patient Information” leaflet with each prescription.

Iss. 3/2010

PATIENT INFORMATION

ENJUVIA®
(synthetic conjugated estrogens, B) Tablets

Read this Patient Information leaflet before you start taking ENJUVIA, and read what you get each time you refill ENJUVIA. There may be new information. This information does not take the place of talking to your healthcare provider about your medical condition or your treatment.

BOXED WARNING

WHAT IS THE MOST IMPORTANT INFORMATION

I SHOULD KNOW ABOUT ENJUVIA (AN ESTROGEN HORMONE MIXTURE)?

- Estrogens increase the chance of getting cancer of the uterus. Report any unusual vaginal bleeding right away while you are taking ENJUVIA. Vaginal bleeding after menopause may be a warning sign of cancer of the uterus (womb). Your healthcare provider should check any unusual vaginal bleeding to find out the cause.
- Do not use estrogens with or without progestins to prevent heart disease, heart attacks, or strokes, or dementia. Using estrogens with or without progestins may increase your chance of getting heart attacks, strokes, breast cancer, and blood clots. Using estrogens, with or without progestins, may increase your risk of dementia, based on a study of women age 65 years or older. You and your healthcare provider should talk regularly about whether you still need treatment with ENJUVIA.

What is ENJUVIA?

ENJUVIA is a medicine that contains a mixture of estrogen hormones.

What is ENJUVIA used for?

ENJUVIA is used after menopause to:

- Reduce moderate to severe hot flashes
  Estrogens are hormones made by a woman's ovaries. The ovaries normally stop making estrogens when a woman is between 45 and 55 years old. This drop in body estrogen levels causes the “change of life” or menopause (the end of monthly menstrual periods). Sometimes, both ovaries are removed during an operation before natural menopause takes place. The sudden drop in estrogen levels causes “surgical menopause.”
  When the estrogen levels begin dropping, some women develop very uncomfortable symptoms, such as feelings of warmth in the face, neck, and chest, or sudden strong feelings of heat and sweating (“hot flashes” or “hot flushes”). In some women, the symptoms are mild, and they will not need estrogens. In other women, symptoms can be more severe. You and your healthcare provider should talk regularly about whether you still need treatment with ENJUVIA.

- Treat moderate to severe vaginal dryness and pain with sex, associated with menopause
  You and your healthcare provider should talk regularly about whether you still need treatment with ENJUVIA to control these problems. If you use ENJUVIA only to treat your vaginal dryness, or pain with sex, talk with your healthcare provider about whether a topical vaginal product might be better for you.

Who should not take ENJUVIA?

Do not start taking ENJUVIA if you:

- Have unusual vaginal bleeding
- Currently have or have had certain cancers
  Estrogens may increase the chances of getting certain types of cancers, including cancer of the breast or uterus. If you have or have had cancer, talk with your healthcare provider about whether you should take ENJUVIA.

- Had a stroke or heart attack in the past year
- Currently have or have had blood clots
- Currently have or have had liver problems
- Are allergic to ENJUVIA or any of its ingredients
  See the end of this leaflet for a list of ingredients in ENJUVIA.

- Think you may be pregnant

Tell your healthcare provider:

- If you are breastfeeding
  The hormones in ENJUVIA can pass into your milk.

- About all of your medical problems
  Your healthcare provider may need to check you more carefully if you have certain conditions, such as asthma (wheezing), epilepsy (seizures), migraine, endometriosis, lupus, or problems with your heart, liver, thyroid, kidneys, or have high calcium levels in your blood.

- About all the medicines you take
  This includes prescription and nonprescription medicines, vitamins, and herbal supplements. Some medicines may affect how ENJUVIA works. ENJUVIA may also affect how your other medicines work.

- If you are going to have surgery or will be on bedrest
  You may need to stop taking estrogens.

How should I take ENJUVIA?

- Take one ENJUVIA tablet by mouth at the same time each day.
- If you miss a dose, take it as soon as possible. If it is almost time for your next dose, skip the missed dose and go back to your normal schedule. Do not take 2 doses at the same time.
- Estrogens should be used at the lowest dose possible for your treatment only as long as needed. You and your healthcare provider should talk regularly (e.g., every 3 to 6 months) about the dose you are taking and whether you still need treatment with ENJUVIA.
- ENJUVIA may be taken with or without food.

What are the possible side effects of estrogens?

Less common but serious side effects include:

- Breast cancer
- Cancer of the uterus
- Stroke
- Heart attack
- Blood clots
- Dementia
- Gallbladder disease
- Ovarian cancer

Some of the warning signs of serious side effects include:

- Breast lumps
- Unusual vaginal bleeding
- Dizziness and faintness
- Changes in speech
- Severe headaches
- Chest pain
- Shortness of breath
- Pains in your legs
- Changes in vision
- Vomiting

Call your healthcare provider right away if you get any of these warning signs, or any other symptoms that concern you.

Common side effects include:

- Headache
- Breast pain
- Irregular vaginal bleeding or spotting
- Stomach/abdominal cramps, bloating
- Nausea and vomiting
- Hair loss

Other side effects include:

- High blood pressure
- Liver problems
- High blood sugar
- Fluid retention
- Enlargement of benign tumors of the uterus (“fibroids”)
- Vaginal yeast infection

These are not all the possible side effects of ENJUVIA. For more information, ask your health-care provider or pharmacist.

What can I do to lower my chances of a serious side effect with ENJUVIA?

- Talk with your healthcare provider regularly about whether you should continue taking ENJUVIA.
- If you have a uterus, talk to your healthcare provider about whether the addition of a progestin is right for you.
- In general, the addition of a progestin is recommended for women with a uterus to reduce the chance of getting cancer of the uterus.
- See your healthcare provider right away if you get vaginal bleeding while taking ENJUVIA.
- Have a breast exam and mammogram (breast X-ray) every year unless your healthcare provider tells you otherwise. If members of your family have had breast cancer or if you have ever had breast lumps or an abnormal mammogram, you may need to have breast exams more often.
- If you have high blood pressure, high cholesterol (fat in the blood), diabetes, are overweight, or if you use tobacco, you may have a higher chance of getting heart disease. Ask your healthcare provider for ways to lower your chance of getting heart disease.

Have an annual gynecologic exam.

General information about safe and effective use of ENJUVIA.

Medicines are sometimes prescribed for conditions that are not mentioned in patient information leaflets. Do not take ENJUVIA for conditions for which it is not prescribed. Do not give ENJUVIA to other people, even if they have the same symptoms you have. It may harm them.

Keep ENJUVIA out of the reach of children.

This leaflet provides a summary of the most important information about ENJUVIA. If you would like more information, talk with your healthcare provider or pharmacist. You can ask for information about ENJUVIA that is written for healthcare professionals.

You may also obtain further information by calling the toll free number 1-877-405-0369 or by visiting our website at www.ENJUVIA.com.

What are the ingredients in ENJUVIA?

ENJUVIA tablets for oral administration are available in 0.3 mg, 0.45 mg, 0.625 mg, 0.9 mg and 1.25 mg strengths of synthetic conjugated estrogens, B. These tablets contain the following inactive ingredients: ascorbyl palmitate, butylated hydroxyanisole, colloidal silicon dioxide, edetate disodium dehydrate, plasticized ethylcellulose, hypromellose, lactose monohydrate, magnesium stearate, purified water, iron oxide red, titanium dioxide, polyethylene glycol, polysorbate 80, triacetate and triacetin/glycerol. In addition, the 0.45 mg tablets contain iron oxide black and iron oxide yellow; the 0.9 mg tablets also contain D&C yellow no. 10 aluminum lake, FD&C blue no. 1 aluminum lake and FD& C yellow no. 6 aluminum lake; and the 1.25 mg tablets contain iron oxide yellow.

Teva Women's Health, Inc.
Subsidiary of Teva Pharmaceuticals USA, Inc.
Sellersville, PA 18960

Iss. 3/2010
11001651

PACKAGE/LABEL PRINCIPAL DISPLAY PANEL - 0.3 mg

0.3 mg

Enjuvia®

(synthetic conjugated estrogens, B) Tablets

PHARMACIST: Dispense the Package Insert provided separately to each patient.

Rx only

Relabeling and Repackaging by:
Physicians Total Care, Inc.
Tulsa, OK 74146

PACKAGE/LABEL PRINCIPAL DISPLAY PANEL - 0.625 mg

0.625 mg

Enjuvia®

(synthetic conjugated estrogens, B) Tablets

PHARMACIST: Dispense the Package Insert provided separately to each patient.

Rx only

PACKAGE/LABEL PRINCIPAL DISPLAY PANEL - 0.9 mg

0.9 mg

Enjuvia®

(synthetic conjugated estrogens, B) Tablets

PHARMACIST: Dispense the Package Insert provided separately to each patient.

Rx only